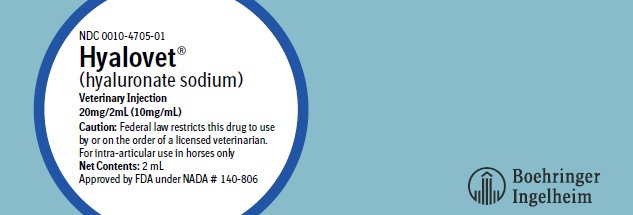 DRUG LABEL: Hyalovet
NDC: 0010-4705 | Form: LIQUID
Manufacturer: Boehringer Ingelheim Animal Health USA Inc.
Category: animal | Type: PRESCRIPTION ANIMAL DRUG LABEL
Date: 20231113

ACTIVE INGREDIENTS: HYALURONATE SODIUM 20 mg/2 mL
INACTIVE INGREDIENTS: SODIUM CHLORIDE 17 mg/2 mL; SODIUM PHOSPHATE, MONOBASIC, DIHYDRATE 0.1 mg/2 mL; SODIUM PHOSPHATE, DIBASIC, DODECAHYDRATE 1.2 mg/2 mL; WATER

Hyalovet®
(hyaluronate sodium)
Veterinary Injection

For intra-articular administration in horses only

Caution:

Federal law restricts this drug to use by or on the order of a licensed veterinarian.

Description:

Hyaluronic acid is the prototype of a wide range of saccharide biopolymers (glycosaminoglycans or mucopolysaccharides) consisting of repeating disaccharide units of N-acetyl-D-glucosamine and D-glucuronic acid linked by beta 1-3 and beta 1-4 glycosidic bonds. A component of all mammalian connective tissue, hyaluronic acid confers viscoelastic and lubricating properties to synovial fluid^1 and structural integrity to cartilage matrix^2. As a therapeutic agent, hyaluronic acid injected into arthritic joints has been shown, in a variety of animal model systems including horses^3, to improve joint function and to activate tissue repair processes in articular cartilage.

Hyalovet (hyaluronate sodium) is clear, colorless, viscous solution of a specific fraction of highly purified hyaluronic acid obtained by a molecular filtration procedure from biological material (rooster combs). The specific hyaluronic acid fraction from which Hyalovet is made has a high degree of molecular definition with an average molecular weight of 500,000-730,000 D.

Each filled 2 mL glass syringe or 2 mL glass vial contains:

Hyaluronate sodium........................................20.0 mg

Sodium chloride..............................................17.0 mg

Monobasic sodium phosphate...........................0.1 mg

Dibasic sodium phosphate.................................1.2 mg

Water for injection.......................................q.s., 2 mL

Indications:

Hyalovet is indicated for the intra-articular treatment of carpal or fetlock joint dysfunction in horses due to acute or chronic, non-infectious synovitis associated with equine osteoarthritis.

Dosage and Administration:

The recommended dose of Hyalovet (hyaluronate sodium) is 2 mL (20 mg hyaluronate sodium) in small or medium sized joints (carpus, fetlock) given by intra-articular injection. More than one joint may be treated at the same time. If necessary, the injection may be repeated after one or more weeks, but not to exceed 2 injections per week for a total of 4 weeks.

Hyalovet should be injected using strict aseptic technique. Excess synovial fluid should be removed prior to injection.

For best results horses should be given two days of rest or limited exercise before resuming normal training.

Contraindications:

There are no known contraindications.

Warning:

Do not use in horses intended for human consumption. Not for human use. Hyalovet Injection must not be administered intravascularly.

Precautions:

Used or partially used syringes should be crushed and disposed of in an approved landfill.

Adverse Reactions:

As with any intra-articular injection a mild inflammatory response (tenderness, heat and swelling) may be seen in the joint following Hyalovet injection. The response is self limiting but may last from two to five days after treatment. If inflammation is excessive or severe, the possibility of infection should be considered and appropriate antibiotic therapy instituted.

To report suspected adverse events, for technical assistance, or to obtain a copy of the Safety Data Sheet, contact Boehringer Ingelheim Animal Health USA Inc. at 1-888-637-4251.

For additional information about adverse drug experience reporting for animal drugs, contact FDA at 1-888-FDA-VETS or online at www.fda.gov/reportanimalae.

Clinical Pharmacology:

Results of gel chromatography studies demonstrate that Hyalovet (hyaluronate sodium) induces aggregation of cartilage proteoglycans sub-units as previously described for other fractions of hyaluronic acid^2. In equine model studies of acute synovitis of the carpal joint, a single intra-articular injection of Hyalovet resulted in statistically significant (p<0.05) functional improvement with regard to lameness, swelling, pain, heat and joint flexion in a dosage dependent fashion. In chronic osteoarthritis secondary to carpal fracture in horses, a single intra-articular injection of 20 mg Hyalovet resulted in statistically significant (p<0.05) reduction in radiopharmaceutical uptake in subchondral bone, as compared to saline injected controls, a finding consistent with reduced inflammation. In controlled clinical trials in horses with lameness due to arthroses of the carpal or fetlock joints, intra-articular injection of 20 mg Hyalovet resulted in marked reduction in clinical lameness, pain on palpation, pain on flexion and facilitated return to training. A measurable and statistically significant (p<0.005) decrease in joint circumference was detected in the horses.

Animal Safety:

In subacute toxicity studies, in horses, intra-articular injection of Hyalovet at the recommended dosage (20 mg/joint) and at 3X and 5X multiples of that dosage, daily for four days followed by twice weekly injections for four additional weeks, resulted in no evidence of toxicity either locally within the joint or systemically in the horses. Slight increases in synovial fluid leucocytes and protein were attributed to the trauma associated with frequent joint injections.

Results of skin testing in horses following repeated intra-articular injections of 40 mg Hyalovet into tibiotarsal joints indicated that the product is non-antigenic in horses; no sensitization was detected.

Storage:

Store at or below 25°C (77° F).

How Supplied:

Hyalovet Veterinary Injection is supplied in a 2 mL syringe or vial containing 20 mg hyaluronate sodium per 2 mL.

NDC 0010-4705-01: 2 mL syringe

NDC 0010-4705-02: 2 mL vial

References:

1. Swann, D.A. et al: Role of hyaluronic acid in joint lubrication. Annals of the Rheumatic Diseases, 33 (1974): 318-326.
2. Hascall, V.C. and Heinegard, D.: Aggregation of cartilage proteoglycans. I. The role of hyaluronic acid. Journal of Biological Chemistry, 249 (1974): 423-433.
3. Gingerich, D.A. et al: Effect of exogenous hyaluronic acid on joint functions in experimentally-induced equine osteoarthritis: dosage titration studies. Research in Veterinary Science, 30 (1981): 192-197.

Hyalovet is a registered trademark of Fidia Farmaceutici S.p.A., Abano Terme, Italy.

Approved by FDA under NADA # 140-806

© 2022 Boehringer Ingelheim Animal Health USA Inc. All rights reserved.

Product of Italy

470501-01

680370/G

Marketed by:

Boehringer Ingelheim Animal Health USA Inc.

Duluth, GA 30096